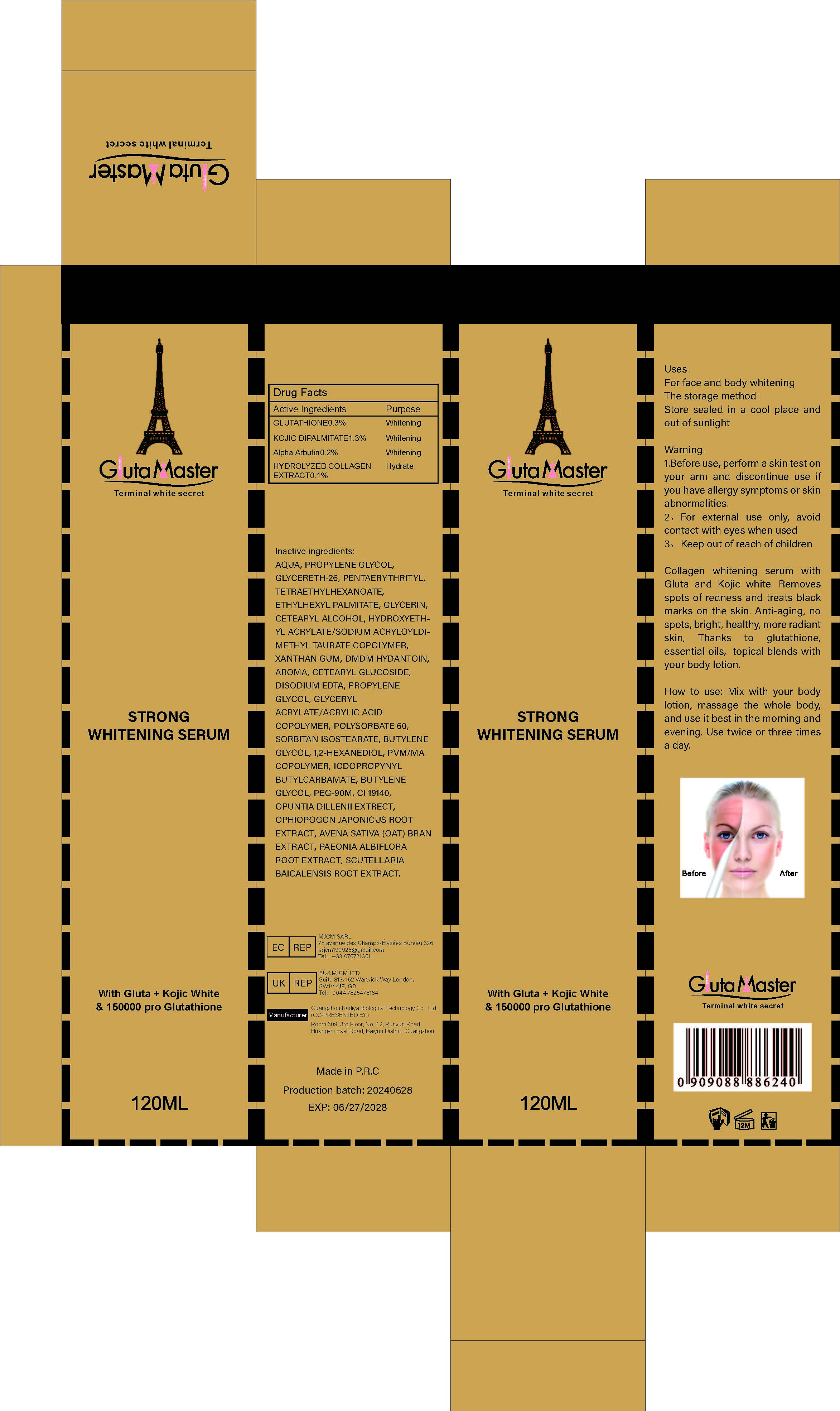 DRUG LABEL: STRONG WHITENING BODY SERUM
NDC: 84423-020 | Form: LIQUID
Manufacturer: Guangzhou Kadiya Biotechnology Co., Ltd.
Category: otc | Type: HUMAN OTC DRUG LABEL
Date: 20240709

ACTIVE INGREDIENTS: KOJIC DIPALMITATE 1.56 mg/120 mg; ALPHA-ARBUTIN 0.24 mg/120 mg; GLUTATHIONE 0.36 mg/120 mg
INACTIVE INGREDIENTS: CETOSTEARYL ALCOHOL; SORBITAN ISOSTEARATE; GLYCERIN; DMDM HYDANTOIN; 1,2-HEXANEDIOL; PROPYLENE GLYCOL; PENTAERYTHRITYL TETRAETHYLHEXANOATE; EDETATE DISODIUM; BUTYLENE GLYCOL; METHYL VINYL ETHER AND MALEIC ANHYDRIDE COPOLYMER (1100000 WAMW); OPHIOPOGON JAPONICUS ROOT; XANTHAN GUM; GLYCERETH-26; PAEONIA LACTIFLORA ROOT; CETEARYL GLUCOSIDE; POLYETHYLENE GLYCOL 4000000; GLYCERYL ACRYLATE/ACRYLIC ACID COPOLYMER (300000 CP AT 2%); IODOPROPYNYL BUTYLCARBAMATE; FD&C YELLOW NO. 5; SCUTELLARIA BAICALENSIS ROOT; POLYSORBATE 60; OAT BRAN; WATER; ETHYLHEXYL PALMITATE; HYDROXYETHYL ACRYLATE/SODIUM ACRYLOYLDIMETHYL TAURATE COPOLYMER (45000 MPA.S AT 1%)

Uses：
For face and body whitening
Indications: For face and body whitening

INACTIVE INGREDIENT

AQUA、PROPYLENE GLYCOL、GLYCERETH-26、PENTAERYTHRITYL、TETRAETHYLHEXANOATE、ETHYLHEXYL PALMITATE、GLYCERIN、CETEARYL ALCOHOL、HYDROXYETHYL ACRYLATE/SODIUM ACRYLOYLDIMETHYL TAURATE COPOLYMER、XANTHAN GUM、DMDM HYDANTOIN、AROMA、CETEARYL GLUCOSIDE、DISODIUM EDTA、PROPYLENE GLYCOL、GLYCERYL ACRYLATE/ACRYLIC ACID COPOLYMER、POLYSORBATE 60、SORBITAN ISOSTEARATE、BUTYLENE GLYCOL、1,2-HEXANEDIOL、PVM/MA COPOLYMER、IODOPROPYNYL BUTYLCARBAMATE、BUTYLENE GLYCOL、PEG-90M、CI 19140、OPUNTIA DILLENII EXTRECT、OPHIOPOGON JAPONICUS ROOT EXTRACT、AVENA SATIVA (OAT) BRAN EXTRACT、PAEONIA ALBIFLORA ROOT EXTRACT、SCUTELLARIA BAICALENSIS ROOT EXTRACT

Warning.
1.Before use, perform a skin test on your arm and discontinue use if you have allergy symptoms or skin abnormalities.
2、For external use only, avoid contact with eyes when used
3、Keep out of reach of children

INACTIVE INGREDIENT

Uses: For face and body whitening

KEEP OUT OF REACH OF CHILDREN SECTION

Drug Facts
Active Ingredients
GLUTATHIONE 0.3%
KOJIC DIPALMITATE 1.3%
Alpha Arbutin 0.2%
HYDROLYZED COLLAGEN EXTRACT 0.1%

DOSAGE AND ADMINISTRATION

PIMENT DOUX is a concentrated, powerful ultra lightener and should be applied to stubborn spots or areas to be lightened. Also add PIMENT DOUX to your cleansing milk TO achieve the desired degree of lightening.

INDICATIONS AND USAGE

Mix with your body lotion, massage the whole body, and use it best in the morning and evening. Use twice or three times a day

Drug Facts
Active Ingredients
GLUTATHIONE 0.3%
KOJIC DIPALMITATE 1.3%
Alpha Arbutin 0.2%
HYDROLYZED COLLAGEN EXTRACT 0.1%

Uses：
For face and body whitening
Indications: For face and body whitening
The storage method：
Store sealed in a cool place and out of sunlight

Warning.
1.Before use, perform a skin test on your arm and discontinue use if you have allergy symptoms or skin abnormalities.
2、For external use only, avoid contact with eyes when used
3、Keep out of reach of children

Inactive ingredients：
AQUA、PROPYLENE GLYCOL、GLYCERETH-26、PENTAERYTHRITYL、TETRAETHYLHEXANOATE、ETHYLHEXYL PALMITATE、GLYCERIN、CETEARYL ALCOHOL、HYDROXYETHYL ACRYLATE/SODIUM ACRYLOYLDIMETHYL TAURATE COPOLYMER、XANTHAN GUM、DMDM HYDANTOIN、AROMA、CETEARYL GLUCOSIDE、DISODIUM EDTA、PROPYLENE GLYCOL、GLYCERYL ACRYLATE/ACRYLIC ACID COPOLYMER、POLYSORBATE 60、SORBITAN ISOSTEARATE、BUTYLENE GLYCOL、1,2-HEXANEDIOL、PVM/MA COPOLYMER、IODOPROPYNYL BUTYLCARBAMATE、BUTYLENE GLYCOL、PEG-90M、CI 19140、OPUNTIA DILLENII EXTRECT、OPHIOPOGON JAPONICUS ROOT EXTRACT、AVENA SATIVA (OAT) BRAN EXTRACT、PAEONIA ALBIFLORA ROOT EXTRACT、SCUTELLARIA BAICALENSIS ROOT EXTRACT